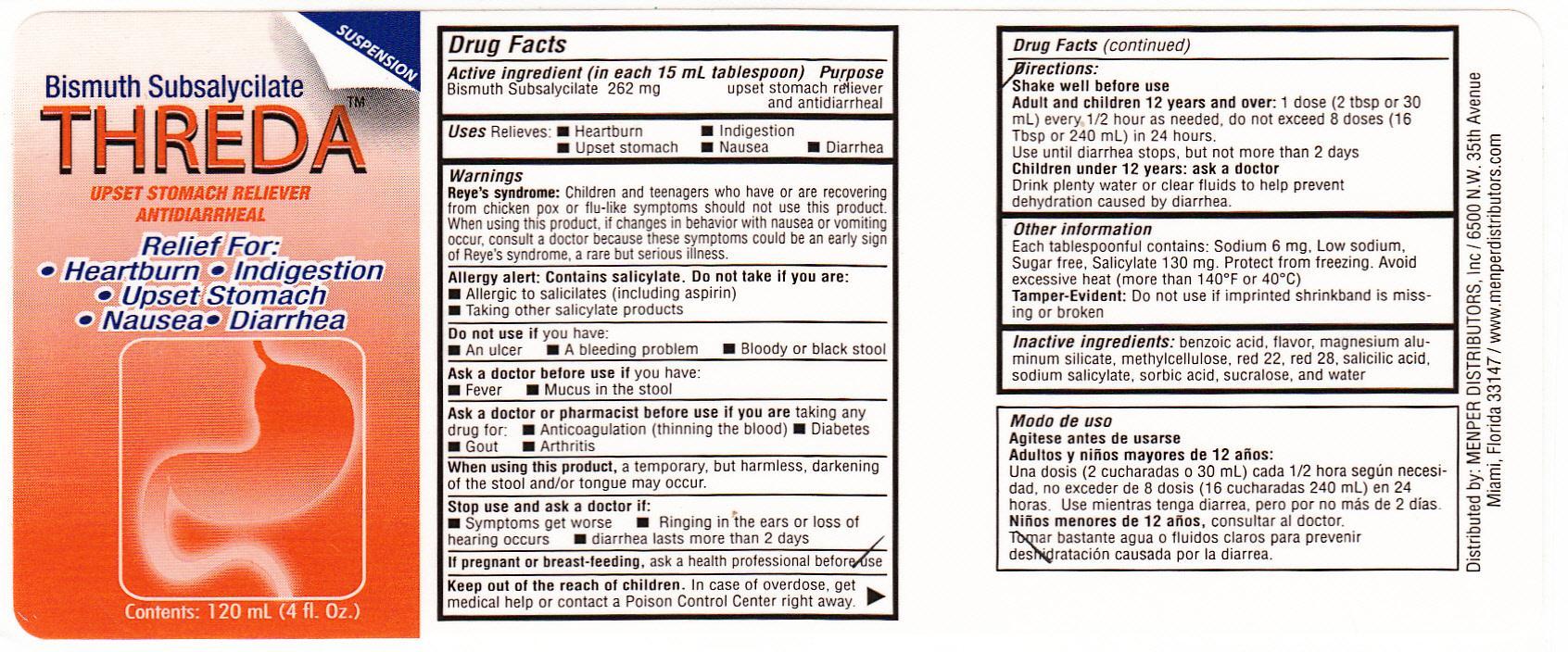 DRUG LABEL: Threda
NDC: 53145-057 | Form: LIQUID
Manufacturer: Menper Distributors, Inc.
Category: otc | Type: HUMAN OTC DRUG LABEL
Date: 20130919

ACTIVE INGREDIENTS: BISMUTH SUBSALICYLATE 262 mg/15 mL
INACTIVE INGREDIENTS: BENZOIC ACID; MAGNESIUM ALUMINUM SILICATE; METHYLCELLULOSE (100 CPS); D&C RED NO. 22; D&C RED NO. 28; SODIUM SALICYLATE; SORBIC ACID; SUCRALOSE; SALICYLIC ACID; WATER

Active Ingredient (in each 15 mL tablespoon)
Bismuth Subsalycilate 262 mg

Purpose
upset stomach reliever and antidiarrheal

Uses

Relieves:

- Heartburn
- Indigestion
- Upset Stomach
- Nausea
- Diarrhea

Warnings
Reye's syndrome: Children and teenagers who have or are recovering from chicken pox or flu-like symptoms should not use this product. When using this product, if changes in behavior with nausea or vomiting occur, consult a doctor because these symptoms could be an early sign of Reye's syndrome, a rare but serious illness.

Allergy Alert: Contains salicylate. Do not take if you are:
Allergic to salicilates (including aspirin) Taking other salicylate products

Do not use if you have:

- An ulcer
- A bleeding problem
- Bloody or black stool

Ask a doctor before useifyou have

- Fever
- Mucus in the stool

Ask a doctor or pharmacist before use if you are taking any drug for:

- Anticoagulation (thinning the blood)
- Diabetes
- Gout
- Arthritis

When using this product, a temporary, but harmless, darkening of the stool and/or tongue may occur.

Stop use and ask a doctor if:

- Symptoms get worse
- Ringing in the ears or loss of hearing occurs
- Diarrhea lasts more than 2 days

PREGNANCY OR BREAST FEEDING

If pregnant or breast-feeding, ask a health professional before use

Keep out of the reach of children.

Directions:
Shake well before use
Adult and children 12 years and over: 1 dose (2tbsp or 30 mL) every 1/2 hour as needed, do not exceed 8 doses (16 Tbsp or 240 mL) in 24 hours.

Use until diarrhea stops, but not more than 2 days.
Children under 12 years: ask a doctor
Drink plenty of water or clear fluids to help prevent dehydration caused by diarrhea.

Other Information
Each tablespoon contains: Sodium 6 mg, Low sodium, Sugar free, Salicylate 130 mg. Protect from freezing. Avoid excessive heat (more than 140°F or 40°C)

Tamper-Evident: Do not use if imprinted shrinkband is missing or broken

Inactive ingredients

BENZOIC ACID, MAGNESIUM ALUMINUM SILICATE, METHYLCELLULOSE (100 CPS), D&C RED NO. 22, D&C RED NO. 28, SALICYLIC ACID, SODIUM SALICYLATE, SORBIC ACID, SUCRALOSE, WATER